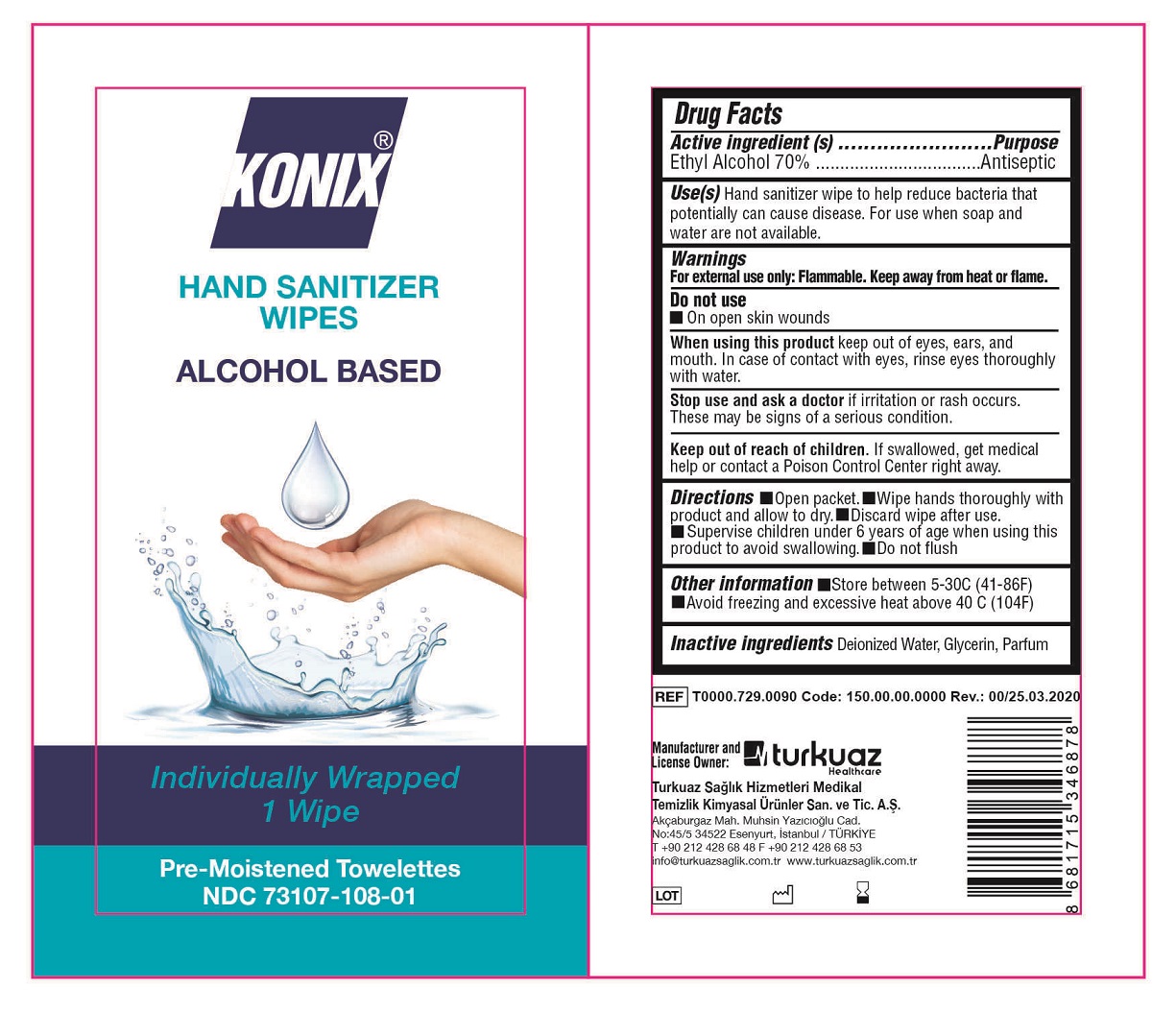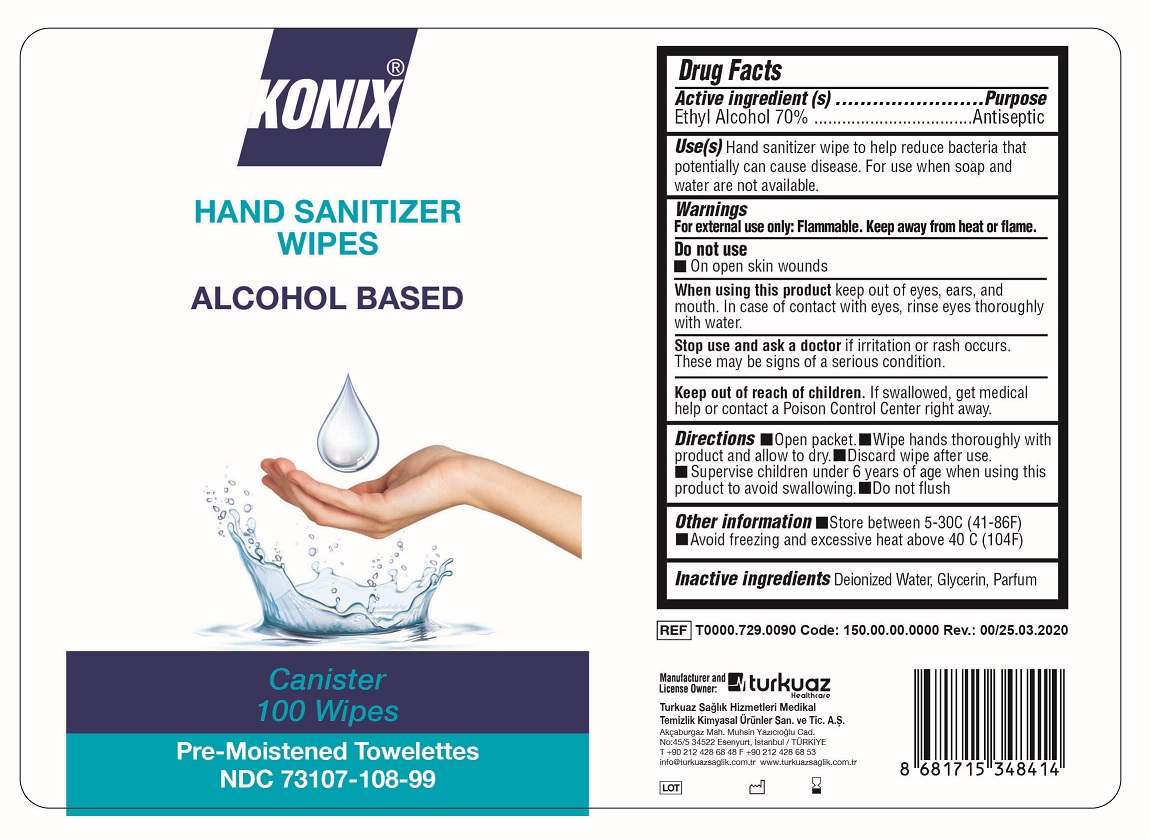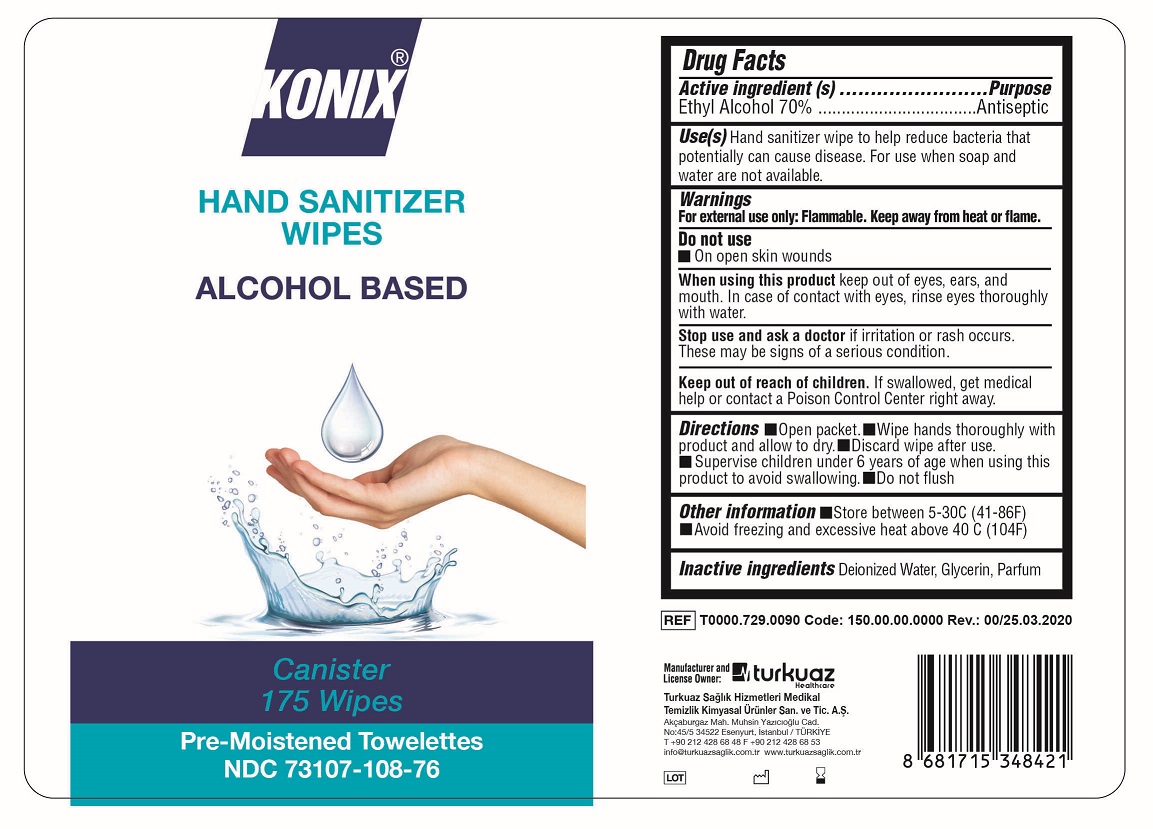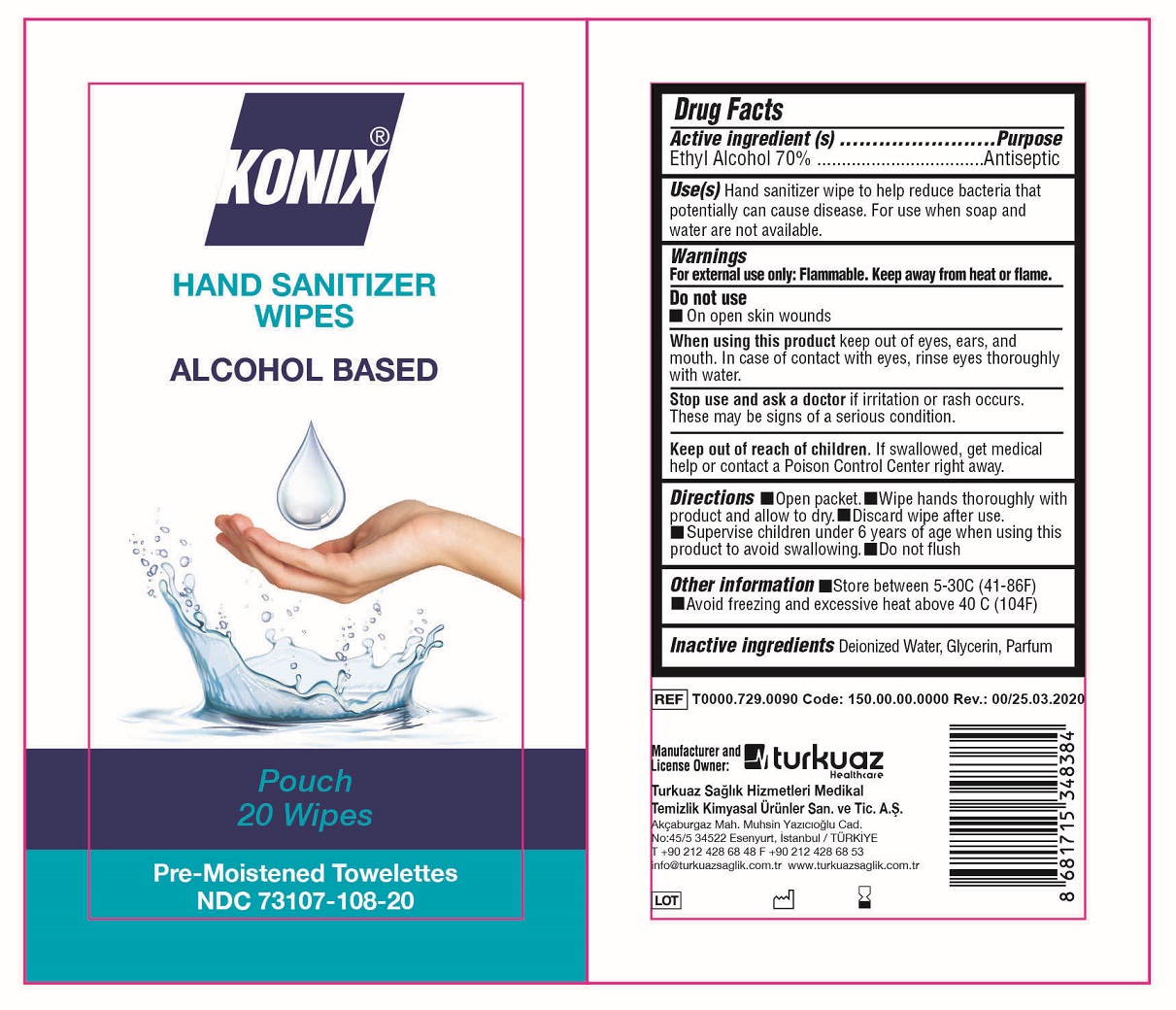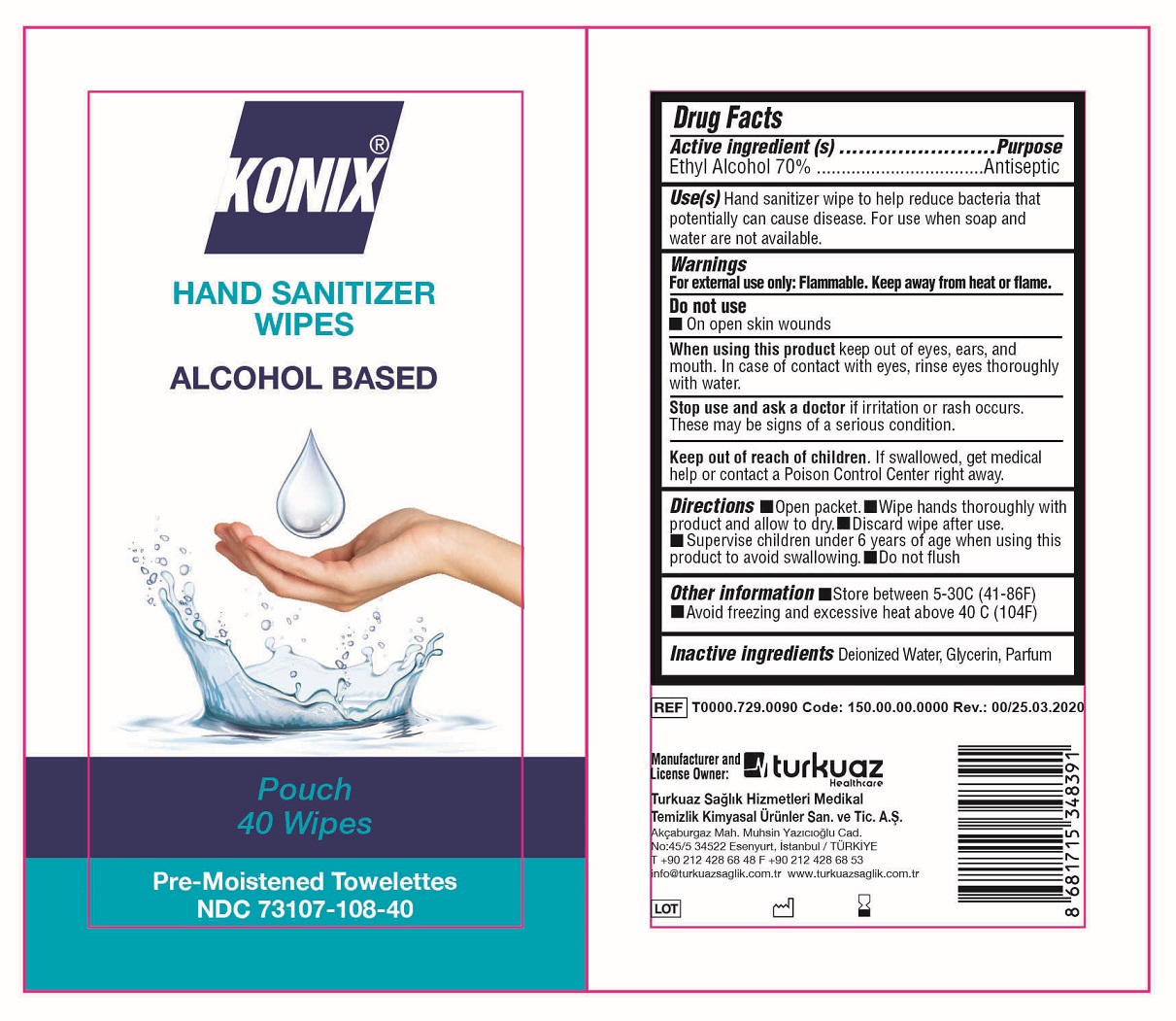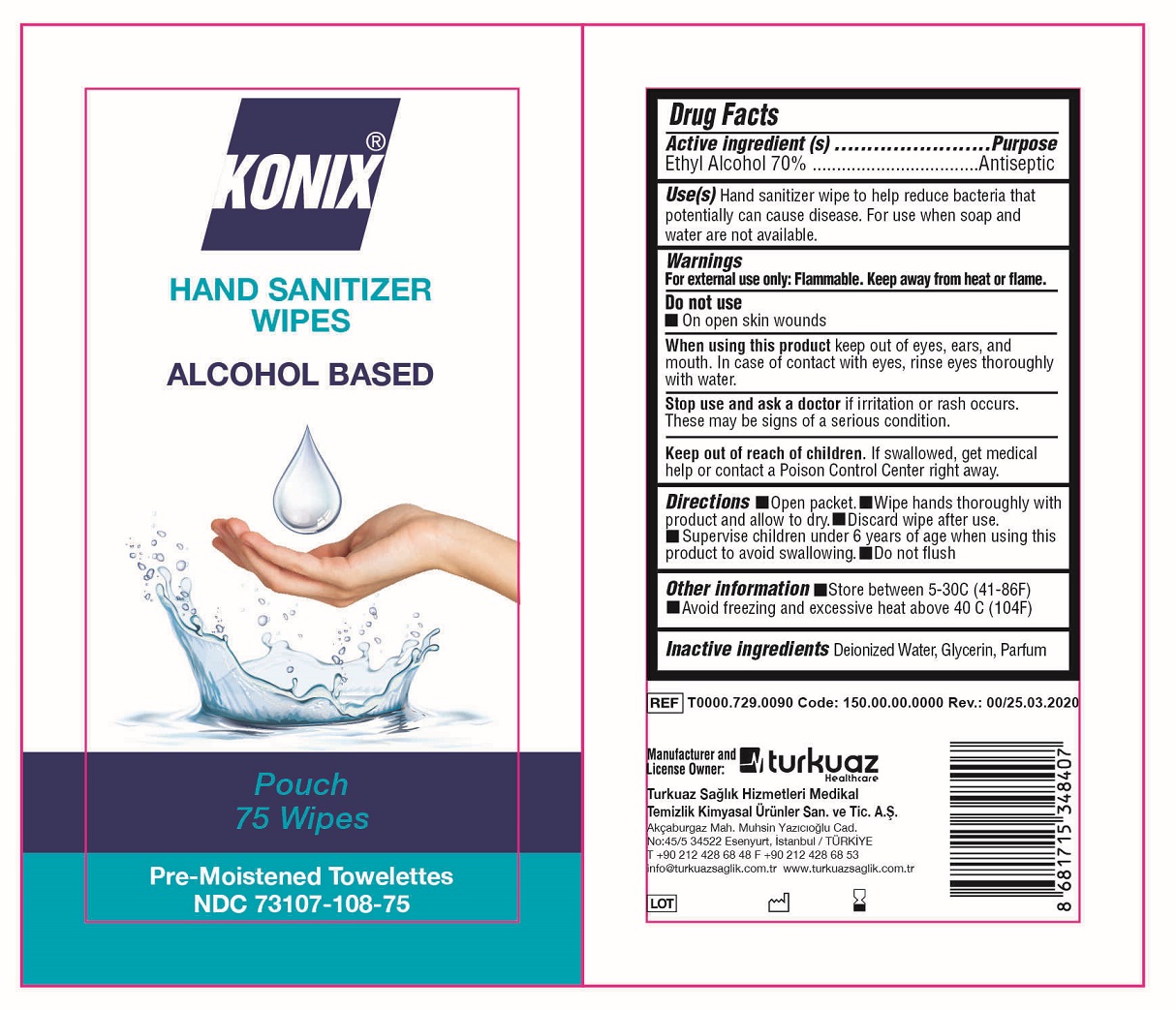 DRUG LABEL: Konix Hand Sanitizer Wipes
NDC: 73107-108 | Form: SWAB
Manufacturer: Turkuaz Saglik Hizmetleri Medikal Temizlik Kimyasal Urunler
Category: otc | Type: HUMAN OTC DRUG LABEL
Date: 20210303

ACTIVE INGREDIENTS: ALCOHOL 70 mL/1 1
INACTIVE INGREDIENTS: WATER; GLYCERIN

Konix Hand Sanitizer Wipes

Active Ingredient(s)

Ethyl Alcohol 70%

Purpose

Antiseptic

Use(s)

Hand sanitizer wipe to help reduce bacteria that potentially can cause disease. For use when soap and water are not available.

For external use only

Flammable. Keep away from open flame and source of heat.

Do not use

on open skin wounds

When using this product

Keep out of eyes, ears and mouth. In case of contact with eyes, rinse eyes thoroughly with water.

Stop use and ask a doctor

if irritation or rash occurs. These may be signs of serious condition.

Keep out of reach of children.

If swallowed, get medical help or contact a Poison Control Center right away

Directions

Open packet. Wipe hands thoroughly with product and allow to dry. Discard wipe after use. Supervise children under 6 years of age when using this product to avoid swallowing. Do not flush.

Other information

Store between room temperature 5-30C (41-86F). Avoid freezing and excessive heat above 40 C (104F).

Inactive ingredients

Deionized water, Glycerine, Fragrance(Parfum)

Konix Hand Sanitizer Wipes

Alcohol Based

Individually Wrapped

1 wipe

Premoistened Towelettes

NDC 73107-108-01

Canister

Konix Hand Sanitizer Wipes

Alcohol Based

Pouch

20 Wipes

PreMoistened Towelettes

NDC 73107-108-20

Konix Hand Sanitizer Wipes

Alcohol Based

Pouch

40 Wipes

PreMoistened Towelettes

NDC 73107-108-40

Konix Hand Sanitizer Wipes

Alcohol Based

Pouch

75 Wipes

PreMoistened Towelettes

NDC 73107-108-75

Konix Hand Sanitizer Wipes

Alcohol Based

Canister

100 Wipes

PreMoistened Towelettes

NDC 73107-108-99

Konix Hand Sanitizer Wipes

Alcohol Based

Canister

175 Wipes

PreMoistened Towelettes

NDC 73107-108-76